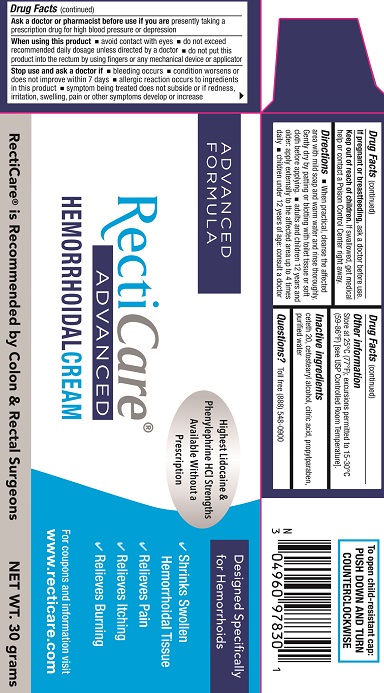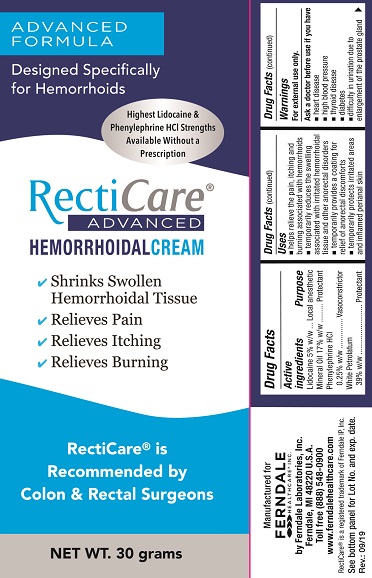 DRUG LABEL: Recticare Advanced
NDC: 0496-0978 | Form: CREAM
Manufacturer: Ferndale Laboratories, Inc.
Category: otc | Type: HUMAN OTC DRUG LABEL
Date: 20241217

ACTIVE INGREDIENTS: LIDOCAINE 50 mg/1 g; MINERAL OIL 170 mg/1 g; PHENYLEPHRINE HYDROCHLORIDE 2.5 mg/1 g; PETROLATUM 390 mg/1 g
INACTIVE INGREDIENTS: CETETH-20; CETOSTEARYL ALCOHOL; ANHYDROUS CITRIC ACID; PROPYLPARABEN; WATER

Recticare Advanced Hemorrhoidal Cream

Active ingredients

Lidocaine 5% w/w
Mineral Oil 17% w/w
Phenylephrine HCl 0.25% w/w
White Petrolatum 39% w/w

Purpose

Lidocaine 5% w/w....................................Local anesthetic
Mineral Oil 17% w/w................................Protectant
Phenylephrine HCl 0.25% w/w.................Vasoconstrictor
White Petrolatum 39% w/w.....................Protectant

Uses

- helps relieve the pain, itching and burning associated with hemorrhoids
- temporarily reduces the swelling associated with irritated hemorrhoidal tissue and other anorectal disorders
- temporarily provides a coating for relief of anorectal discomforts
- temporarily protects irritated areas and inflamed perianal skin

Warnings

For external use only.

Ask a doctor before use if you have

- heart disease
- high blood pressure
- thyroid disease
- diabetes
- difficulty in urination due to enlargement of the prostate gland

Ask a doctor or pharmacist before use if you are

presently taking a prescription drug for high blood pressure or depression

When using this product

- avoid contact with eyes
- do not exceed recommended daily dosage unless directed by a doctor
- do not put this product into the rectum by using fingers or any mechanical device or applicator

Stop use and ask a doctor if

- bleeding occurs
- condition worsens or does not improve within 7 days
- allergic reaction occurs to ingredients in this product
- symptom being treated does not subside or if redness, irritation, swelling, pain or other symptoms develop or increase

If pregnant or breastfeeding,

ask a doctor before use.

Keep out of reach of children.

If swallowed, get medical help or contact a Poison Control Center right away.

Directions

- When practical, cleanse the affected area with mild soap and warm water and rinse thoroughly. Gently dry by patting or blotting with toilet tissue or soft cloth before applying.
- adults and children 12 years and older: apply externally to the affected area up to 4 times daily
- children under 12 years of age: consult a doctor
- To use finger cots: Roll one finger cot over finger. Gently squeeze cream onto finger cot. Smooth a layer of the cream over affected area.

Other information

Store at 25°C (77°F); excursions permitted to 15-30°C (59-86°F) [see USP Controlled Room Temperature]

Inactive ingredients

ceteth 20, cetostearyl alcohol, citric acid, propylparaben, purified water